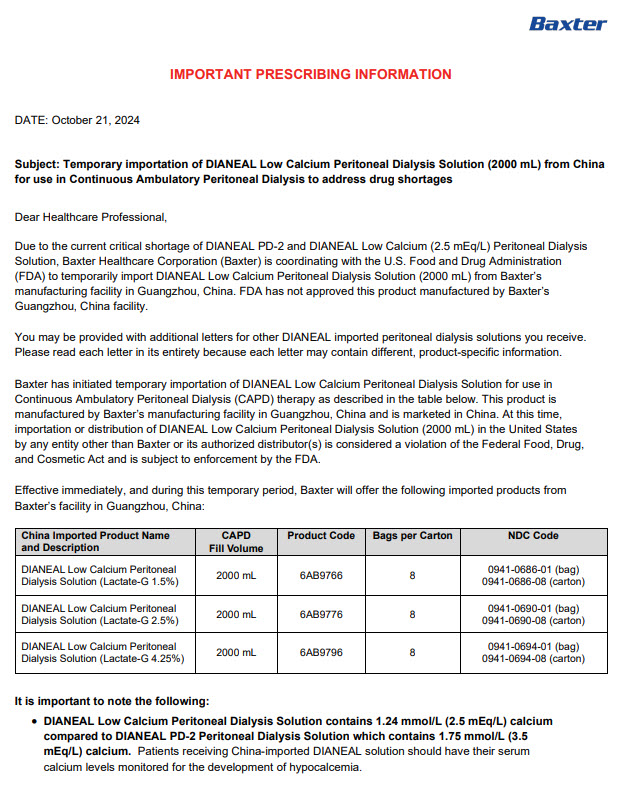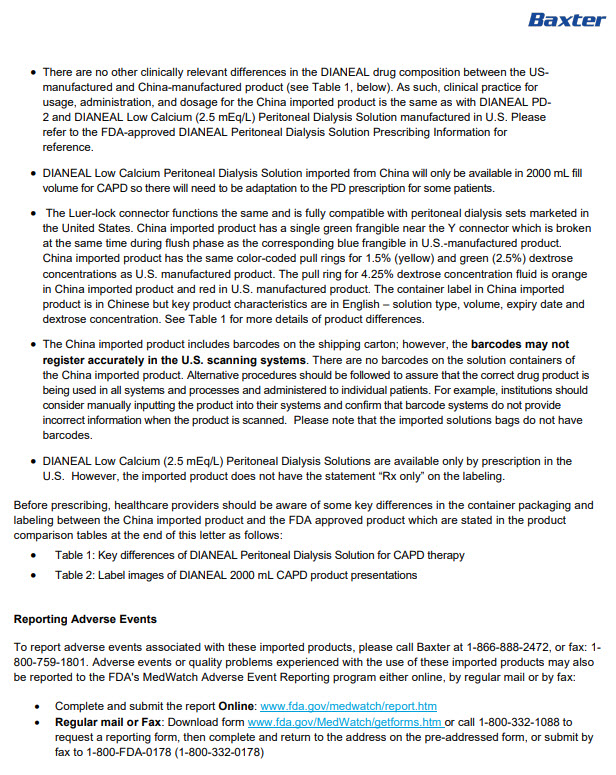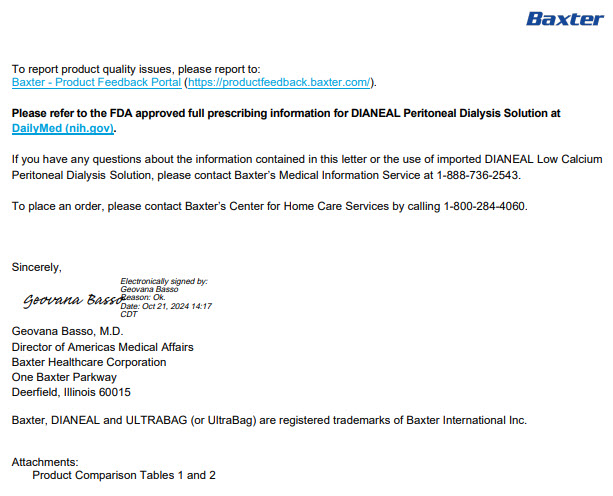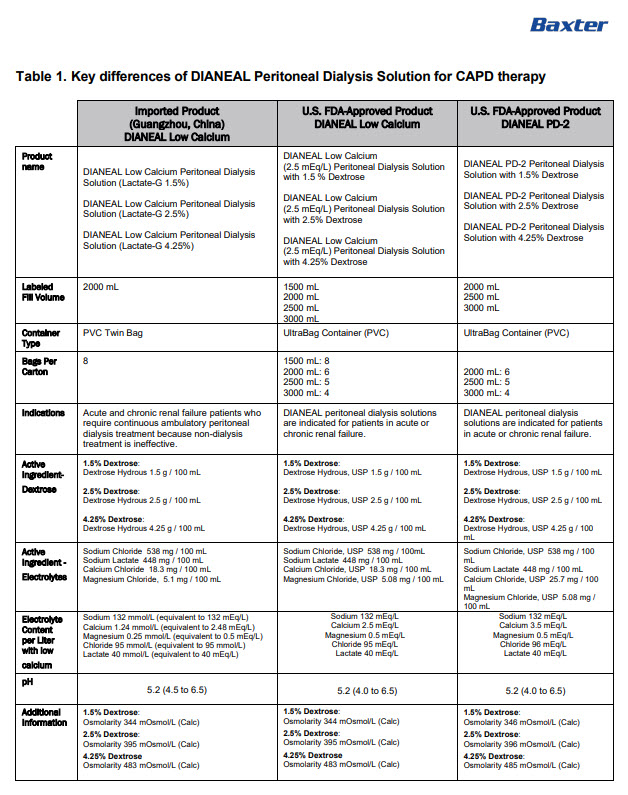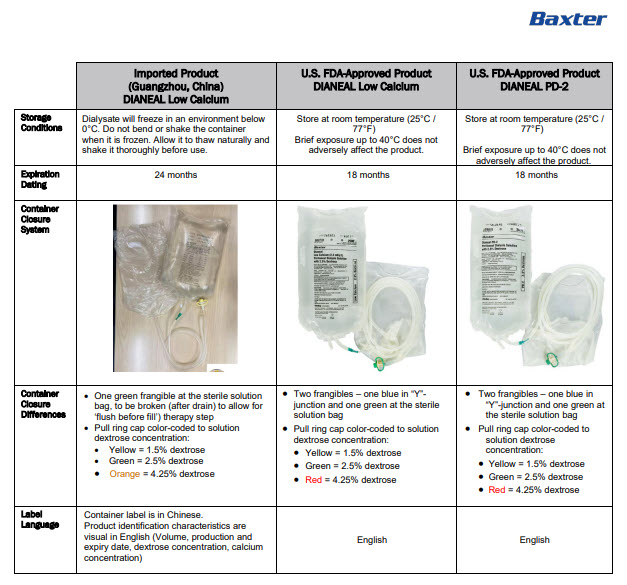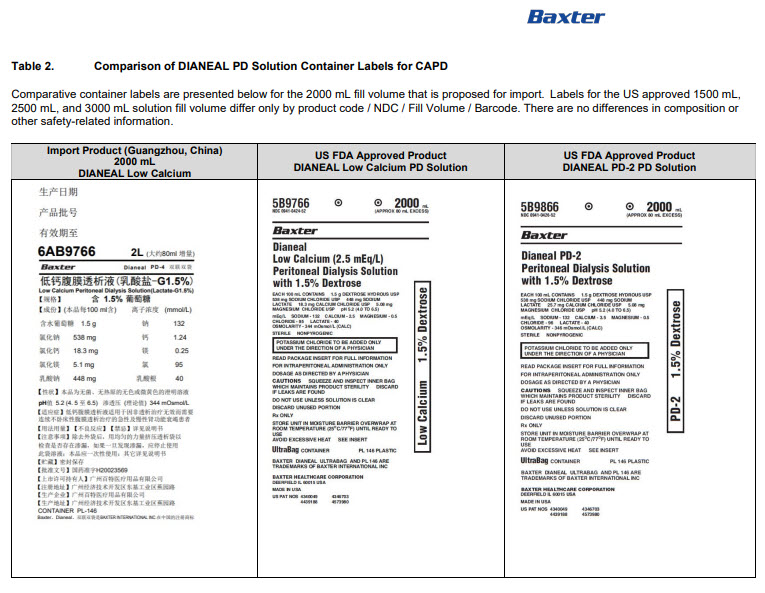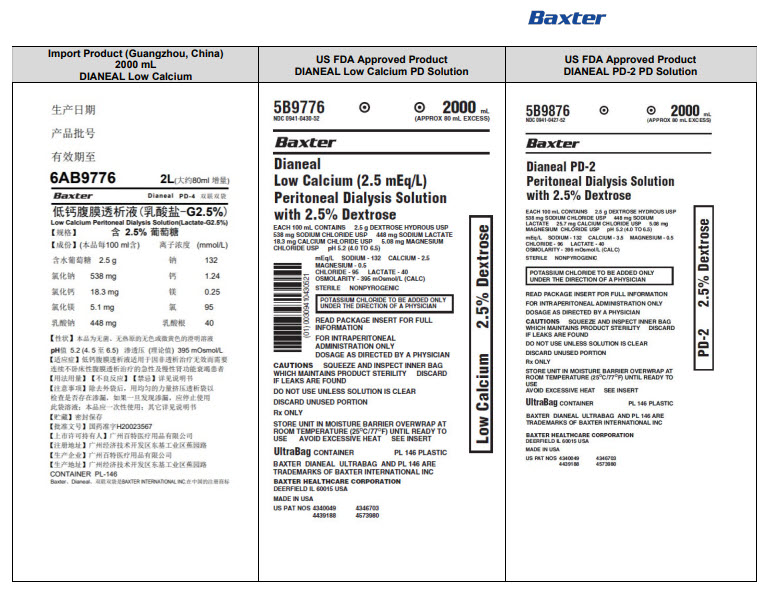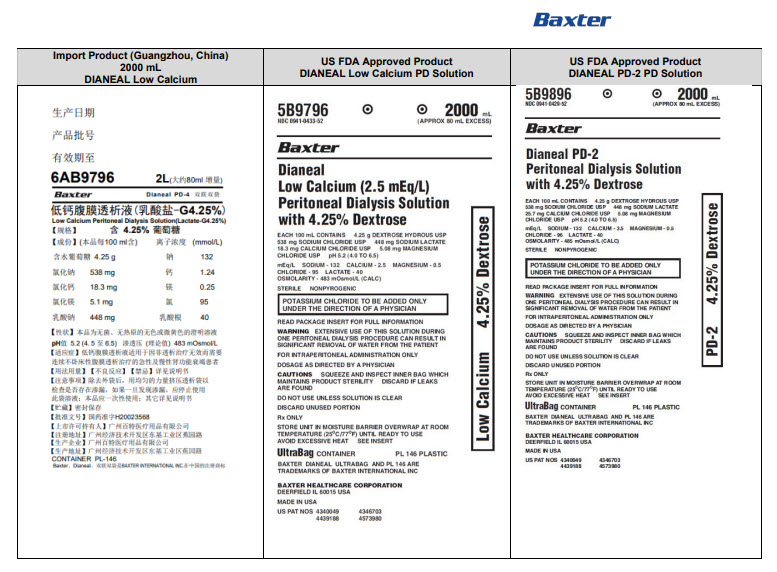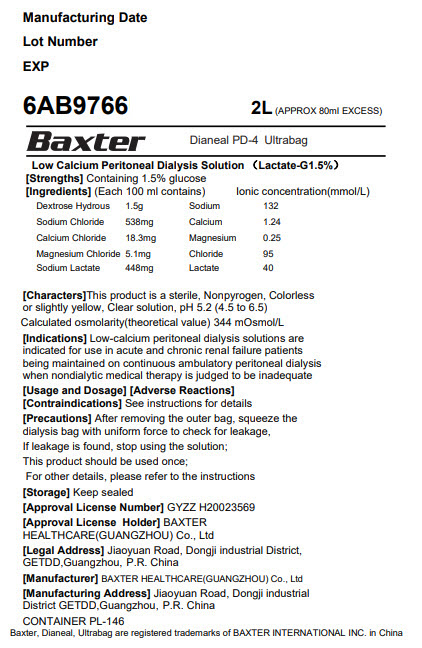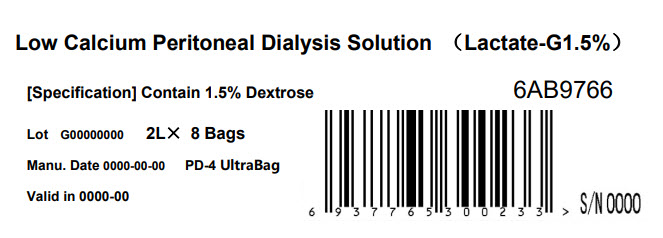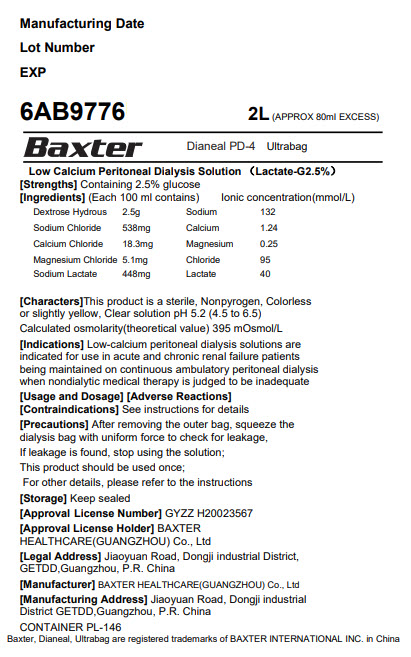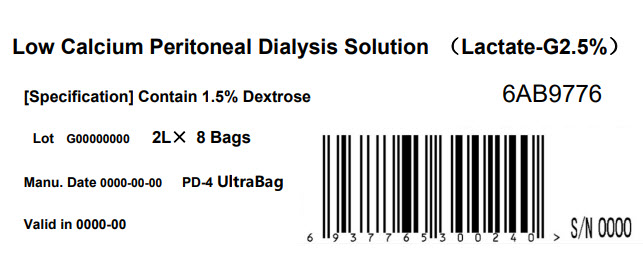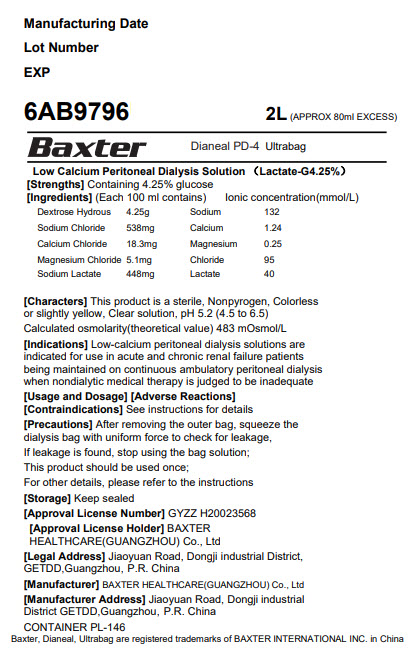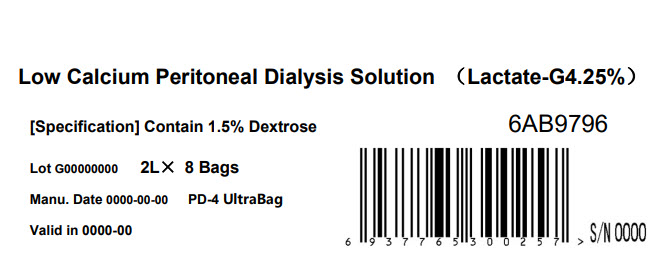 DRUG LABEL: DIANEAL LOW CALCIUM WITH DEXTROSE
NDC: 0941-0686 | Form: INJECTION, SOLUTION
Manufacturer: Vantive US Healthcare LLC
Category: prescription | Type: HUMAN PRESCRIPTION DRUG LABEL
Date: 20250509

ACTIVE INGREDIENTS: DEXTROSE MONOHYDRATE 1.5 g/100 mL; SODIUM CHLORIDE 538 mg/100 mL; SODIUM LACTATE 448 mg/100 mL; CALCIUM CHLORIDE 18.3 mg/100 mL; MAGNESIUM CHLORIDE 5.1 mg/100 mL
INACTIVE INGREDIENTS: WATER

DIANEAL Low Calcium with Dextrose

PACKAGE/LABEL PRINCIPAL DISPLAY PANEL

Manufacturing Date

Lot Number

EXP

6AB9766 2L (APPROX 80ml EXCESS)
BaxterLogo Dianeal PD-4 Ultrabag
Low Calcium Peritoneal Dialysis Solution (Lactate-G1.5%)
[Strengths]Containing 1.5% glucose
[Ingredients](Each 100 ml contains) Ionic concentration(mmol/L)

Dextrose Hydrous | 1.5 g | Sodium | 132
Sodium Chloride | 538mg | Calcium | 1.24
Calcium Chloride | 18.3mg | Magnesium | 0.25
Magnesium Chloride | 5.1mg | Chloride | 95
Sodium Lactate | 448mg | Lactate | 40

[Characters]This product is a sterile, Nonpyrogen, Colorless
or slightly yellow, Clear solution, pH 5.2 (4.5 to 6.5)

Calculated osmolarity(theoretical value) 344 mOsmol/L

[Indications]Low-calcium peritoneal dialysis solutions are
indicated for use in acute and chronic renal failure patients
being maintained on continuous ambulatory peritoneal dialysis
when nondialytic medical therapy is judged to be inadequate

[Usage and Dosage] [Adverse Reactions]
[Contraindications] See instructions for details

[Precautions]After removing the outer bag, squeeze the
dialysis bag with uniform force to check for leakage,
If leakage is found, stop using the solution;
This product should be used once;
For other details, please refer to the instructions

[Storage]Keep sealed
[Approval License Number]GYZZ H20023569
[Approval License Holder]BAXTER
HEALTHCARE(GUANGZHOU) Co., Ltd

[Legal Address]Jiaoyuan Road, Dongji industrial District,
GETDD, Guangzhou, P.R. China

[Manufacturer]BAXTER HEALTHCARE(GUANGZHOU) Co., Ltd
[Manufacturing Address]Jiaoyuan Road, Dongji industrial
District GETDD,Guangzhou, P.R. China

CONTAINER PL-146
Baxter, Dianeal, Ultrabag are registered trademarks of BAXTER INTERNATIONAL INC. in China

Low Calcium Peritoneal Dialysis Solution (Lactate-G1.5%)

[Specification] Contain 1.5% Dextrose 6AB9766

Lot G00000000 2LX 8 Bags

Manu. Date 0000-00-00 PD-4 UltraBag

Valid in 0000-00

Barcode
6 9 3 7 7 6 5 3 0 0 2 3 3 >

S/N 0000

Manufacturing Date

Lot Number

EXP

6AB9776 2L (APPROX 80ml EXCESS)
BaxterLogo Dianeal PD-4 Ultrabag
Low Calcium Peritoneal Dialysis Solution (Lactate-G2.5%)
[Strengths]Containing 2.5% glucose
[Ingredients](Each 100 ml contains) Ionic concentration(mmol/L)

Dextrose Hydrous | 2.5 g | Sodium | 132
Sodium Chloride | 538mg | Calcium | 1.24
Calcium Chloride | 18.3mg | Magnesium | 0.25
Magnesium Chloride | 5.1mg | Chloride | 95
Sodium Lactate | 448mg | Lactate | 40

[Characters]This product is a sterile, Nonpyrogen, Colorless
or slightly yellow, Clear solution, pH 5.2 (4.5 to 6.5)

Calculated osmolarity(theoretical value) 395 mOsmol/L

[Indications]Low-calcium peritoneal dialysis solutions are
indicated for use in acute and chronic renal failure patients
being maintained on continuous ambulatory peritoneal dialysis
when nondialytic medical therapy is judged to be inadequate

[Usage and Dosage] [Adverse Reactions]
[Contraindications] See instructions for details

[Precautions]After removing the outer bag, squeeze the
dialysis bag with uniform force to check for leakage,
If leakage is found, stop using the solution;
This product should be used once;
For other details, please refer to the instructions

[Storage]Keep sealed
[Approval License Number]GYZZ H20023567
[Approval License Holder]BAXTER
HEALTHCARE(GUANGZHOU) Co., Ltd

[Legal Address]Jiaoyuan Road, Dongji industrial District,
GETDD, Guangzhou, P.R. China

[Manufacturer]BAXTER HEALTHCARE(GUANGZHOU) Co., Ltd
[Manufacturing Address]Jiaoyuan Road, Dongji industrial
District GETDD,Guangzhou, P.R. China

CONTAINER PL-146
Baxter, Dianeal, Ultrabag are registered trademarks of BAXTER INTERNATIONAL INC. in China

Low Calcium Peritoneal Dialysis Solution (Lactate-G2.5%)

[Specification] Contain 1.5% Dextrose 6AB9776

Lot G00000000 2LX 8 Bags

Manu. Date 0000-00-00 PD-4 UltraBag

Valid in 0000-00

Barcode
6 9 3 7 7 6 5 3 0 0 2 4 0 >

S/N 0000

Manufacturing Date

Lot Number

EXP

6AB9796 2L (APPROX 80ml EXCESS)
BaxterLogo Dianeal PD-4 Ultrabag
Low Calcium Peritoneal Dialysis Solution (Lactate-G4.25%)
[Strengths]Containing 4.25% glucose
[Ingredients](Each 100 ml contains) Ionic concentration(mmol/L)

Dextrose Hydrous | 4.25 g | Sodium | 132
Sodium Chloride | 538mg | Calcium | 1.24
Calcium Chloride | 18.3mg | Magnesium | 0.25
Magnesium Chloride | 5.1mg | Chloride | 95
Sodium Lactate | 448mg | Lactate | 40

[Characters]This product is a sterile, Nonpyrogen, Colorless
or slightly yellow, Clear solution, pH 5.2 (4.5 to 6.5)

Calculated osmolarity(theoretical value) 483 mOsmol/L

[Indications]Low-calcium peritoneal dialysis solutions are
indicated for use in acute and chronic renal failure patients
being maintained on continuous ambulatory peritoneal dialysis
when nondialytic medical therapy is judged to be inadequate

[Usage and Dosage] [Adverse Reactions]
[Contraindications] See instructions for details

[Precautions]After removing the outer bag, squeeze the
dialysis bag with uniform force to check for leakage,
If leakage is found, stop using the solution;
This product should be used once;
For other details, please refer to the instructions

[Storage]Keep sealed
[Approval License Number]GYZZ H20023568
[Approval License Holder]BAXTER
HEALTHCARE(GUANGZHOU) Co., Ltd

[Legal Address]Jiaoyuan Road, Dongji industrial District,
GETDD, Guangzhou, P.R. China

[Manufacturer]BAXTER HEALTHCARE(GUANGZHOU) Co., Ltd
[Manufacturing Address]Jiaoyuan Road, Dongji industrial
District GETDD,Guangzhou, P.R. China

CONTAINER PL-146
Baxter, Dianeal, Ultrabag are registered trademarks of BAXTER INTERNATIONAL INC. in China

Low Calcium Peritoneal Dialysis Solution (Lactate-G4.25%)

[Specification] Contain 1.5% Dextrose 6AB9796

Lot G00000000 2LX 8 Bags

Manu. Date 0000-00-00 PD-4 UltraBag

Valid in 0000-00

Barcode
6 9 3 7 7 6 5 3 0 0 2 5 7 >

S/N 0000